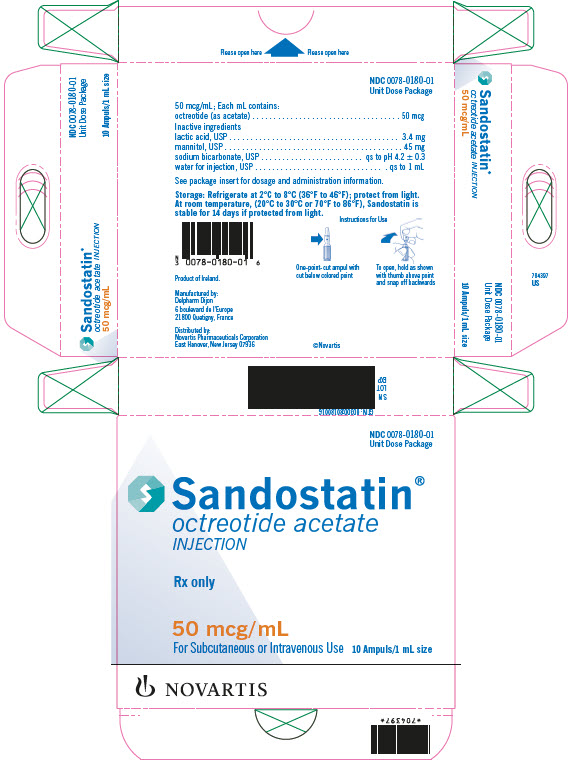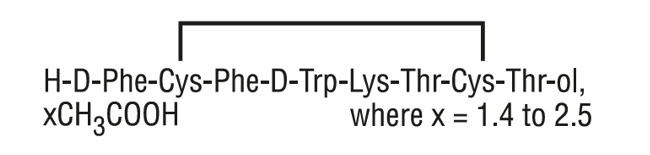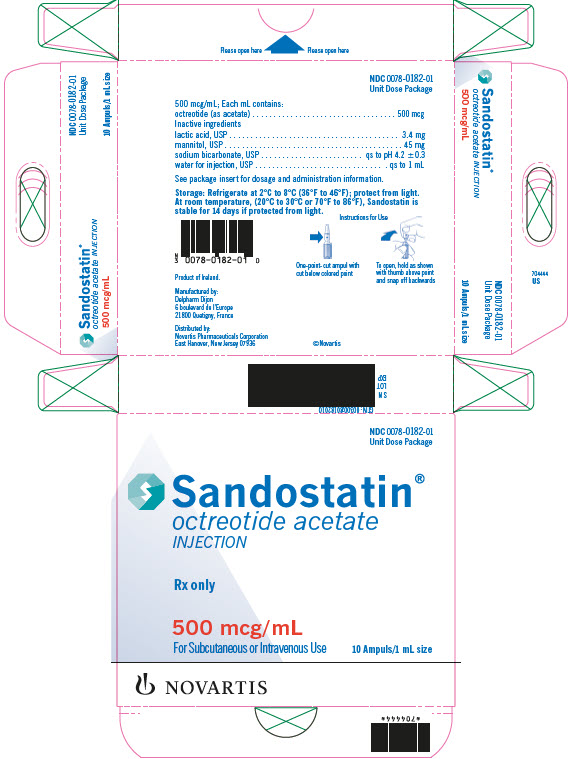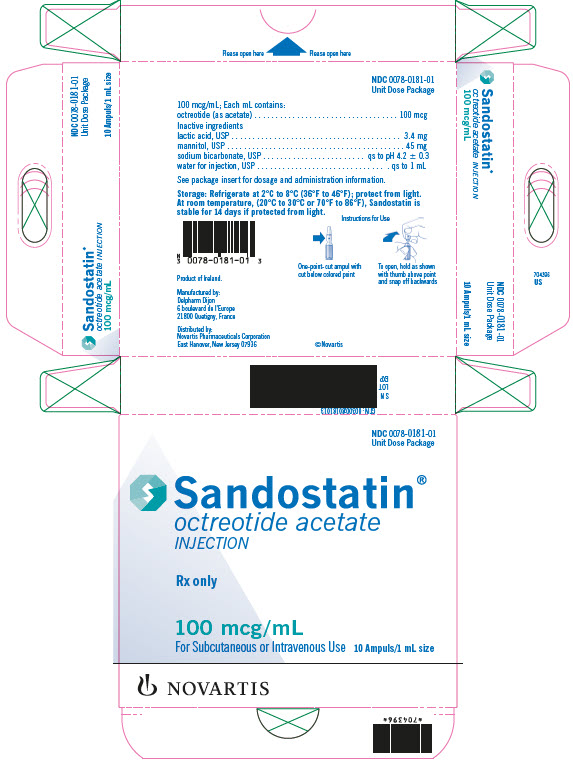 DRUG LABEL: Sandostatin
NDC: 0078-0180 | Form: INJECTION, SOLUTION
Manufacturer: Novartis Pharmaceuticals Corporation
Category: prescription | Type: HUMAN PRESCRIPTION DRUG LABEL
Date: 20250811

ACTIVE INGREDIENTS: OCTREOTIDE ACETATE 50 ug/1 mL
INACTIVE INGREDIENTS: LACTIC ACID 3.4 mg/1 mL; MANNITOL 45 mg/1 mL; SODIUM BICARBONATE; WATER

HIGHLIGHTS OF PRESCRIBING INFORMATION

These highlights do not include all the information needed to use SANDOSTATIN INJECTION safely and effectively. See full prescribing information for SANDOSTATIN INJECTION.
SANDOSTATIN® (octreotide acetate) INJECTION, for subcutaneous or intravenous use
Initial U.S. Approval: 1988

RECENT MAJOR CHANGES

Warnings and Precautions, Steatorrhea and Malabsorption of Dietary Fats (5.5) | 7/2024

1 INDICATIONS AND USAGE

Sandostatin Injection is a somatostatin analogue indicated:

- Acromegaly: To reduce blood levels of growth hormone (GH) and insulin growth factor-1 (IGF-1; somatomedin C) in acromegaly patients who have had inadequate response to or cannot be treated with surgical resection, pituitary irradiation, and bromocriptine mesylate at maximally tolerated doses. (1.1)
- Carcinoid Tumors: For the symptomatic treatment of patients with metastatic carcinoid tumors where it suppresses or inhibits the severe diarrhea and flushing episodes associated with the disease. (1.2)
- Vasoactive Intestinal Peptide Tumors (VIPomas): For the treatment of profuse watery diarrhea associated with VIP-secreting tumors. (1.3)

Limitations of Use

Improvement in clinical signs and symptoms, or reduction in tumor size or rate of growth, were not shown in clinical trials performed with Sandostatin Injection; these trials were not optimally designed to detect such effects. (1.4)

2 DOSAGE AND ADMINISTRATION

- Sandostatin Injection may be administered subcutaneously or intravenously. (2.1)
- Acromegaly: Recommended initial Sandostatin dosage is 50 mcg three times daily during the initial 2 weeks of therapy. Maintenance dose 100 mcg to 500 mcg three times daily. (2.2)
- Carcinoid Tumors: Recommended dosage range of 100 mcg to 600 mcg daily in two to four divided doses during the initial 2 weeks of therapy. (2.3)
- VIPomas: Recommended dosage range of 200 mcg to 300 mcg daily in two to four divided doses during the initial 2 weeks of therapy. (2.4)

3 DOSAGE FORMS AND STRENGTHS

Injection: 50 mcg/mL, 100 mcg/mL, or 500 mcg/mL of octreotide (as acetate) in a single-dose ampul. (3)

4 CONTRAINDICATIONS

- Sensitivity to this drug or any of its components. (4)

5 WARNINGS AND PRECAUTIONS

- Cardiac Function Abnormalities: Increased risk for higher degree of atrioventricular blocks. Consider cardiac monitoring in patients receiving Sandostatin Injection intravenously. Bradycardia, arrhythmias, or conduction abnormalities may occur. Use with caution in at-risk patients. Dosage adjustment of cardiac medications may be necessary. (5.1)
- Cholelithiasis and Complications of Cholelithiasis: Monitor periodically. Discontinue if complications of cholelithiasis are suspected. (5.2)
- Glucose Metabolism: Hypoglycemia or hyperglycemia may occur. Glucose monitoring is recommended and anti-diabetic treatment may need adjustment. (5.3)
- Thyroid Function: Hypothyroidism may occur. Monitor thyroid levels periodically. (5.4)
- Steatorrhea and Malabsorption of Dietary Fats: New onset steatorrhea, stool discoloration, loose stools, abdominal bloating, and weight loss may occur. If new occurrence or worsening of these symptoms are reported, evaluate for potential pancreatic exocrine insufficiency. (5.5)

6 ADVERSE REACTIONS

Most common adverse reactions (incidence > 10%) in patients with acromegaly are gallbladder abnormalities, sinus bradycardia, diarrhea, loose stools, nausea, abdominal discomfort, hyperglycemia, and hypothyroidism. In other patients, most common adverse reactions (incidence > 10%) are gallbladder abnormalities. (6.1)

To report SUSPECTED ADVERSE REACTIONS, contact Novartis Pharmaceuticals Corporation at 1-888-669-6682 or FDA at 1-800-FDA-1088 or www.fda.gov/medwatch.

7 DRUG INTERACTIONS

- The following drugs require monitoring and possible dose adjustment when used with Sandostatin Injection: Cyclosporine, insulin, oral hypoglycemic agents, beta-blockers, and bromocriptine. (7)
- Lutetium Lu 177 Dotatate Injection: Discontinue Sandostatin Injection at least 24 hours prior to each lutetium Lu 177 dotatate dose. (7.6)

8 USE IN SPECIFIC POPULATIONS

- Females and Males of Reproductive Potential: Advise premenopausal females of the potential for an unintended pregnancy. (8.3)

FULL PRESCRIBING INFORMATION

1 INDICATIONS AND USAGE

1.1 Acromegaly

Sandostatin Injection is indicated to reduce blood levels of growth hormone (GH) and insulin growth factor-1 (IGF-1; somatomedin C) in acromegaly patients who have had inadequate response to or cannot be treated with surgical resection, pituitary irradiation, and bromocriptine mesylate at maximally tolerated doses.

1.2 Carcinoid Tumors

Sandostatin Injection is indicated for treatment of severe diarrhea and flushing episodes associated with metastatic carcinoid tumors.

1.3 Vasoactive Intestinal Peptide Tumors

Sandostatin Injection is indicated for the treatment of the profuse watery diarrhea associated with vasoactive intestinal peptide tumors (VIPomas)-secreting tumors.

1.4 Important Limitations of Use

Improvement in clinical signs and symptoms, or reduction in tumor size or rate of growth, were not shown in clinical trials performed with Sandostatin Injection; these trials were not optimally designed to detect such effects.

2 DOSAGE AND ADMINISTRATION

2.1 Dosage and Administration Overview

- Sandostatin Injection may be administered subcutaneously or intravenously. Pain with subcutaneous administration may be reduced by using the smallest volume that will deliver the desired dose. Sites should be rotated in a systematic manner.
- Parenteral drug products should be inspected visually for particulate matter and discoloration prior to administration. Do not use if particulates and/or discoloration are observed. Sandostatin Injection is not compatible in Total Parenteral Nutrition solutions because of the formation of a glycosyl octreotide conjugate which may decrease the efficacy of the product.
- Sandostatin Injection may be diluted in volumes of 50 mL to 200 mL and infused intravenously over 15 to 30 minutes or administered by intravenous (IV) push over 3 minutes. In emergency situations (e.g., carcinoid crisis), it may be given by rapid bolus.
- Assess total and/or free T4 levels at baseline and periodically during chronic Sandostatin therapy.

2.2 Recommended Dosage and Monitoring for Acromegaly

The recommended initial dosage of Sandostatin is 50 mcg three times daily to be administered subcutaneously. Increase Sandostatin dose based upon GH or IGF-1 levels. The goal is to achieve GH levels less than 5 ng/mL or IGF-1 levels within normal range. Monitor GH or IGF-1 every two weeks after initiating Sandostatin therapy or with dosage change, and to guide titration.

The most common dosage is 100 mcg three times daily, but some patients require up to 500 mcg three times daily for maximum effectiveness. Doses greater than 300 mcg/day seldom result in additional biochemical benefit, and if an increase in dose fails to provide additional benefit, the dose should be reduced.

Sandostatin Injection should be withdrawn yearly for approximately 4 weeks from patients who have received irradiation to assess disease activity. If GH or IGF-1 levels increase and signs and symptoms recur, Sandostatin Injection therapy may be resumed.

2.3 Recommended Dosage and Monitoring for Carcinoid Tumors

The recommended daily dosage of Sandostatin Injection during the first 2 weeks of therapy ranges from 100 to 600 mcg/day in two to four divided doses given subcutaneously (mean daily dosage is 300 mcg). In the clinical studies, the median daily maintenance dosage was approximately 450 mcg, but clinical and biochemical benefits were obtained in some patients with as little as 50 mcg, while others required doses up to 1500 mcg/day. However, experience with doses above 750 mcg/day is limited. Measurement of urinary 5-hydroxyindole acetic acid, plasma serotonin, plasma Substance P may be useful in monitoring the progress of therapy.

2.4 Recommended Dosage and Monitoring for Vasoactive Intestinal Peptide Tumors

Daily dosages of 200 mcg to 300 mcg in two to four divided doses given subcutaneously are recommended during the initial 2 weeks of therapy (range, 150 mcg to 750 mcg) to control symptoms of the disease. On an individual basis, dosage may be adjusted to achieve a therapeutic response, but usually doses above 450 mcg/day are not required. Measurement of Plasma vasoactive intestinal peptide (VIP) may be useful in monitoring the progress of therapy.

3 DOSAGE FORMS AND STRENGTHS

Injection: 50 mcg/mL, 100 mcg/mL, or 500 mcg/mL of octreotide (as acetate) as a clear solution in a single-dose ampul.

4 CONTRAINDICATIONS

Sensitivity to this drug or any of its components.

5 WARNINGS AND PRECAUTIONS

5.1 Cardiac Function Abnormalities

Complete Atrioventricular Block

Patients who receive Sandostatin Injection intravenously may be at increased risk for higher degree atrioventricular blocks. In postmarketing reports, complete atrioventricular block was reported in patients receiving IV Sandostatin Injection during surgical procedures. In the majority of patients, Sandostatin Injection was given at higher than recommended doses and/or as a continuous IV infusion. The safety of continuous IV infusion has not been established in patients receiving Sandostatin Injection for the approved indications. Consider cardiac monitoring in patients receiving Sandostatin Injection intravenously.

Other Cardiac Conduction Abnormalities

Other cardiac conduction abnormalities have occurred during treatment with Sandostatin Injection. In acromegalic patients, bradycardia (< 50 bpm) developed in 25%; conduction abnormalities occurred in 10% and arrhythmias occurred in 9% of patients during Sandostatin Injection therapy [see Adverse Reactions (6)]. Other electrocardiogram (ECG) changes observed included QT prolongation, axis shifts, early repolarization, low voltage, R/S transition, and early R-wave progression. These ECG changes are not uncommon in acromegalic patients. Dose adjustments in drugs, such as beta-blockers that have bradycardia effects may be necessary. In one acromegalic patient with severe congestive heart failure (CHF), initiation of Sandostatin Injection therapy resulted in worsening of CHF with improvement when drug was discontinued. Confirmation of a drug effect was obtained with a positive rechallenge.

5.2 Cholelithiasis and Complications of Cholelithiasis

Sandostatin Injection may inhibit gallbladder contractility and decrease bile secretion, which may lead to gallbladder abnormalities or sludge. Acute cholecystitis, ascending cholangitis, biliary obstruction, cholestatic hepatitis, or pancreatitis have been reported with Sandostatin Injection therapy. In clinical trials (primarily patients with acromegaly or psoriasis), the incidence of biliary tract abnormalities was 63% (27% gallstones, 24% sludge without stones, 12% biliary duct dilatation). The incidence of stones or sludge in patients who received Sandostatin Injection for 12 months or longer was 52%. Less than 2% of patients treated with Sandostatin Injection for 1 month or less developed gallstones. One patient developed ascending cholangitis during Sandostatin Injection therapy and died. If complications of cholelithiasis are suspected, discontinue Sandostatin Injection and treat appropriately.

5.3 Hyperglycemia and Hypoglycemia

Sandostatin Injection alters the balance between the counter-regulatory hormones, insulin, glucagon and GH, which may result in hypoglycemia or hyperglycemia. The hypoglycemia or hyperglycemia which occurs during Sandostatin Injection therapy is usually mild but may result in overt diabetes mellitus or necessitate dose changes in insulin or other anti-diabetic agents. Hypoglycemia and hyperglycemia occurred on Sandostatin Injection in 3% and 16% of acromegalic patients, respectively [see Adverse Reactions (6)]. Severe hyperglycemia, subsequent pneumonia, and death following initiation of Sandostatin Injection therapy was reported in one patient with no history of hyperglycemia.

Monitor glucose levels during Sandostatin Injection therapy. Adjust dosing of insulin or other anti-diabetic therapy accordingly.

5.4 Thyroid Function Abnormalities

Octreotide suppresses secretion of thyroid stimulating hormone (TSH), which may result in hypothyroidism. Baseline and periodic assessment of thyroid function (TSH, total, and/or free T4) is recommended during chronic therapy [see Adverse Reactions (6)].

5.5 Steatorrhea and Malabsorption of Dietary Fats

New onset steatorrhea, stool discoloration and loose stools have been reported in patients receiving somatostatin analogs, including Sandostatin. Somatostatin analogs reversibly inhibit secretion of pancreatic enzymes and bile acids, which may result in malabsorption of dietary fats and subsequent symptoms of steatorrhea, loose stools, abdominal bloating, and weight loss. If new occurrence or worsening of these symptoms are reported in patients receiving Sandostatin, evaluate patients for potential pancreatic exocrine insufficiency and manage accordingly.

5.6 Changes in Vitamin B12 Levels

Depressed vitamin B12 levels and abnormal Schilling’s tests have been observed in some patients receiving Sandostatin Injection therapy, and monitoring of vitamin B12 levels is recommended during Sandostatin Injection therapy.

6 ADVERSE REACTIONS

The following clinically significant adverse reactions are described elsewhere in the labeling:

- Complete Atrioventricular Block [see Warnings and Precautions (5.1)]
- Cholelithiasis and Complications of Cholelithiasis [see Warnings and Precautions (5.2)]
- Hyperglycemia and Hypoglycemia [see Warnings and Precautions (5.3)]
- Thyroid Function Abnormalities [see Warnings and Precautions (5.4)]
- Steatorrhea and Malabsorption of Dietary Fats [see Warnings and Precautions (5.5)]
- Changes in Vitamin B12 Levels [see Warnings and Precautions (5.6)]

6.1 Clinical Trials Experience

Because clinical trials are conducted under widely varying conditions, adverse reaction rates observed in the clinical trials of a drug cannot be directly compared to rates in the clinical trials of another drug and may not reflect the rates observed in practice.

Gallbladder Abnormalities

Gallbladder abnormalities, especially stones and/or biliary sludge, frequently develop in patients on chronic Sandostatin Injection therapy [see Warnings and Precautions (5.1)]. In clinical trials (primarily patients with acromegaly or psoriasis), the incidence of biliary tract abnormalities was 63% (27% gallstones, 24% sludge without stones, 12% biliary duct dilatation). The incidence of stones or sludge in patients who received Sandostatin Injection for 12 months or longer was 52%. Less than 2% of patients treated with Sandostatin Injection for 1 month or less developed gallstones.

Cardiac

In acromegalics, sinus bradycardia (< 50 bpm) developed in 25%; conduction abnormalities occurred in 10% and arrhythmias developed in 9% of patients during Sandostatin Injection therapy [see Warnings and Precautions (5.1)].

Gastrointestinal

Diarrhea, loose stools, nausea, and abdominal discomfort were each seen in 34% to 61% of acromegalic patients in U.S. studies. 2.6% of the patients discontinued therapy due to these symptoms. These symptoms were seen in 5% to 10% of patients with carcinoid tumors and VIPomas.

The frequency of these symptoms was not dose related, but diarrhea and abdominal discomfort generally resolved more quickly in patients treated with 300 mcg/day than in those treated with 750 mcg/day. Vomiting, flatulence, abnormal stools, abdominal distention, and constipation were each seen in less than 10% of patients.

In rare instances, gastrointestinal side effects may resemble acute intestinal obstruction, with progressive abdominal distension, severe epigastric pain, abdominal tenderness, and guarding.

Hypo/Hyperglycemia

Hypoglycemia and hyperglycemia occurred in 3% and 16% of acromegalic patients, respectively, but only in about 1.5% of other patients. Symptoms of hypoglycemia were noted in approximately 2% of patients.

Hypothyroidism

In acromegalics, biochemical hypothyroidism alone occurred in 12% while goiter occurred in 8% and 4% required initiation of thyroid replacement therapy during Sandostatin Injection therapy [see Warnings and Precautions (5.4)]. In patients without acromegaly, hypothyroidism has only been reported in several isolated patients and goiter has not been reported.

Other Adverse Events

Pain on injection was reported in 7.7%, headache in 6%, and dizziness in 5%. Pancreatitis was also observed [see Warnings and Precautions (5.2)].

Other Adverse Events 1% to 4%

Other events, each observed in 1% to 4% of patients, included fatigue, weakness, pruritus, joint pain, backache, urinary tract infection, cold symptoms, flu symptoms, injection site hematoma, bruise, edema, flushing, blurred vision, pollakiuria, fat malabsorption, hair loss, visual disturbance, and depression.

Anaphylactoid reactions, including anaphylactic shock, have been reported in several patients receiving Sandostatin Injection.

6.2 Postmarketing Experience

The following adverse reactions have been identified during postapproval use of Sandostatin Injection. Because these reactions are reported voluntarily from a population of uncertain size, it is not always possible to reliably estimate their frequency or establish a causal relationship to drug exposure.

Hepatobiliary: cholelithiasis, cholecystitis, cholangitis and pancreatitis, which have sometimes required cholecystectomy

Gastrointestinal: intestinal obstruction, pancreatic exocrine insufficiency

Hematologic: thrombocytopenia

7 DRUG INTERACTIONS

7.1 Cyclosporine

Octreotide has been associated with alterations in nutrient absorption, so it may have an effect on absorption of orally administered drugs. Concomitant administration of Sandostatin Injection with cyclosporine may decrease blood levels of cyclosporine and result in transplant rejection.

7.2 Insulin and Oral Hypoglycemic Drugs

Octreotide inhibits the secretion of insulin and glucagon. Therefore, blood glucose levels should be monitored when Sandostatin Injection treatment is initiated or when the dose is altered and anti-diabetic treatment should be adjusted accordingly.

7.3 Bromocriptine

Concomitant administration of octreotide and bromocriptine increases the availability of bromocriptine.

7.4 Other Concomitant Drug Therapy

Concomitant administration of bradycardia-inducing drugs (e.g., beta-blockers) may have an additive effect on the reduction of heart rate associated with octreotide. Dose adjustments of concomitant medication may be necessary.

Octreotide has been associated with alterations in nutrient absorption, so it may have an effect on absorption of orally administered drugs.

7.5 Drug Metabolism Interactions

Limited published data indicate that somatostatin analogs might decrease the metabolic clearance of compounds known to be metabolized by cytochrome P450 enzymes, which may be due to the suppression of GH. Since it cannot be excluded that octreotide may have this effect, other drugs mainly metabolized by CYP3A4 and which have a low therapeutic index (e.g., quinidine, terfenadine) should therefore be used with caution.

7.6 Lutetium Lu 177 Dotatate Injection

Octreotide competitively binds to somatostatin receptors and may interfere with the efficacy of lutetium Lu 177 dotatate. Discontinue Sandostatin Injection at least 24 hours prior to each lutetium Lu 177 dotatate dose.

8 USE IN SPECIFIC POPULATIONS

8.1 Pregnancy

Risk Summary

The limited data with Sandostatin Injection in pregnant women are insufficient to inform a drug-associated risk for major birth defects and miscarriage. In animal reproduction studies, no adverse developmental-effects were observed with IV administration of octreotide to pregnant rats and rabbits during organogenesis at doses 7- and 13-times, respectively the maximum recommended human dose (MRHD) of 1.5 mg/day based on body surface area (BSA). Transient growth retardation, with no impact on postnatal development, was observed in rat offspring from a pre- and post-natal study of octreotide at IV doses below the MRHD based on BSA (see Data).

The estimated background risk of major birth defects and miscarriage for the indicated population is unknown. In the U.S. general population, the estimated background risk of major birth defects and miscarriage in clinically recognized pregnancies is 2% to 4% and 15% to 20%, respectively.

Data

Human Data

In postmarketing data, a limited number of exposed pregnancies have been reported in patients with acromegaly. Most women were exposed to octreotide during the first trimester of pregnancy at doses ranging from 100 to 300 mcg/day of Sandostatin Injection or 20 mg to 30 mg once a month of octreotide acetate for injectable suspension, however some women elected to continue octreotide therapy throughout pregnancy. In cases with a known outcome, no congenital malformations were reported.

Animal Data

In embryo-fetal development studies in rats and rabbits, pregnant animals received IV doses of octreotide up to 1 mg/kg/day during the period of organogenesis. A slight reduction in body weight gain was noted in pregnant rats at 0.1 and 1 mg/kg/day. There were no maternal effects in rabbits or embryo-fetal effects in either species up to the maximum dose tested. At 1 mg/kg/day in rats and rabbits, the dose multiple was approximately 7- and 13-times, respectively, at the highest recommended human dose of 1.5 mg/day based on BSA.

In a pre- and post-natal development rat study at IV doses of 0.02-1 mg/kg/day, a transient growth retardation of the offspring was observed at all doses which was possibly a consequence of GH inhibition by octreotide. The doses attributed to the delayed growth are below the human dose of 1.5 mg/day, based on BSA.

8.2 Lactation

Risk Summary

There is no information available on the presence of Sandostatin Injection in human milk, the effects of the drug on the breastfed infant, or the effects of the drug on milk production. Studies show that octreotide administered subcutaneously passes into the milk of lactating rats; however, due to species-specific differences in lactation physiology, animal data may not reliably predict drug levels in human milk (see Data). The developmental and health benefits of breastfeeding should be considered along with the mother’s clinical need for Sandostatin Injection, and any potential adverse effects on the breastfed child from Sandostatin Injection or from the underlying maternal condition.

Data

Following a subcutaneous dose (1 mg/kg) of octreotide to lactating rats, transfer of octreotide into milk was observed at a low concentration compared to plasma (milk/plasma ratio of 0.009).

8.3 Females and Males of Reproductive Potential

Discuss the potential for unintended pregnancy with premenopausal women as the therapeutic benefits of a reduction in GH levels and normalization of insulin-like growth factor 1 (IGF-1) concentration in acromegalic females treated with octreotide may lead to improved fertility.

8.4 Pediatric Use

Safety and efficacy of Sandostatin Injection in the pediatric population have not been demonstrated.

No formal controlled clinical trials have been performed to evaluate the safety and effectiveness of Sandostatin Injection in pediatric patients under age 6 years. In postmarketing reports, serious adverse events, including hypoxia, necrotizing enterocolitis, and death, have been reported with Sandostatin Injection use in children, most notably in children under 2 years of age. The relationship of these events to octreotide has not been established as the majority of these pediatric patients had serious underlying co-morbid conditions.

The efficacy and safety of Sandostatin Injection using the octreotide acetate for injectable suspension formulation was examined in a single randomized, double-blind, placebo-controlled, 6 month pharmacokinetics study in 60 pediatric patients age 6 to 17 years with hypothalamic obesity resulting from cranial insult. The mean octreotide concentration after 6 doses of 40 mg octreotide acetate for injectable suspension administered by intramuscular (IM) injection every 4 weeks was approximately 3 ng/mL. Steady-state concentrations was achieved after 3 injections of a 40-mg dose. Mean body mass index (BMI) increased 0.1 kg/m^2 in octreotide acetate for injectable suspension-treated subjects compared to 0.0 kg/m^2 in saline control-treated subjects. Efficacy was not demonstrated. Diarrhea occurred in 11 of 30 (37%) patients treated with octreotide acetate for injectable suspension. No unexpected adverse events were observed. However, with octreotide acetate for injectable suspension at 40 mg once a month, the incidence of new cholelithiasis in this pediatric population (33%) was higher than that seen in other adult indications, such as acromegaly (22%) or malignant carcinoid syndrome (24%), where octreotide acetate for injectable suspension was 10 mg to 30 mg once a month.

8.5 Geriatric Use

Clinical studies of Sandostatin Injection did not include sufficient numbers of subjects aged 65 and over to determine whether they respond differently from younger subjects. Other reported clinical experience has not identified differences in responses between the elderly and younger patients. In general, dose selection for an elderly patient should be cautious, usually starting at the low end of the dosing range, reflecting the greater frequency of decreased hepatic, renal, or cardiac function, and of concomitant disease or other drug therapy.

8.6 Renal Impairment

In patients with severe renal failure requiring dialysis, the half-life of Sandostatin may be increased, necessitating adjustment of the maintenance dosage [see Clinical Pharmacology (12.3)].

8.7 Hepatic Impairment-Cirrhotic Patients

In patients with liver cirrhosis, the half-life of the drug may be increased, necessitating adjustment of the maintenance dosage [see Clinical Pharmacology (12.3)].

10 OVERDOSAGE

A limited number of accidental overdoses of Sandostatin Injection in adults have been reported. In adults, the doses ranged from 2,400 to 6,000 mcg/day administered by continuous infusion (100 to 250 mcg/hour) or subcutaneously (1,500 mcg 3 times a day). Adverse events in some patients included arrhythmia, complete atrioventricular block, hypotension, cardiac arrest, brain hypoxia, pancreatitis, hepatitis steatosis, hepatomegaly, lactic acidosis, flushing, diarrhea, lethargy, weakness, and weight loss.

If overdose occurs, symptomatic management is indicated. Up-to-date information about the treatment of overdose can often be obtained from the National Poison Control Center at 1-800-222-1222.

11 DESCRIPTION

Sandostatin Injection, a cyclic octapeptide prepared as a clear sterile solution of octreotide, acetate salt, in a buffered lactic acid solution for administration by deep subcutaneous or IV injection. Octreotide acetate, known chemically as L-Cysteinamide, D-phenylalanyl-L-cysteinyl-L-phenylalanyl-D-tryptophyl-L-lysyl-L-threonyl-N-[2-hydroxy-1-(hydroxymethyl)propyl]-,cyclic (2 → 7)-disulfide; [R-(R*, R*)] acetate salt, is a long-acting octapeptide with pharmacologic actions mimicking those of the natural hormone somatostatin.

Sandostatin Injection is available as sterile 1-mL ampuls in 3 strengths, containing 50 mcg, 100 mcg, or 500 mcg octreotide (as acetate). Each ampul also contains lactic acid, USP (3.4 mg), mannitol, USP (45 mg), sodium bicarbonate, USP (quantity sufficient to pH 4.2 ± 0.3), water for injection, USP (quantity sufficient to 1 mL).

Lactic acid and sodium bicarbonate are added to provide a buffered solution, pH to 4.2 ± 0.3.

The molecular weight of octreotide acetate is 1019.3 g/mol (free peptide, C49H66N10O10S2) and its amino acid sequence is:

12 CLINICAL PHARMACOLOGY

12.1 Mechanism of Action

Sandostatin Injection exerts pharmacologic actions similar to the natural hormone, somatostatin. It is an even more potent inhibitor of GH, glucagon, and insulin than somatostatin. Like somatostatin, it also suppresses luteinizing hormone (LH) response to gonadotropin releasing hormone (GnRH), decreases splanchnic blood flow, and inhibits release of serotonin, gastrin, VIP, secretin, motilin, and pancreatic polypeptide.

By virtue of these pharmacological actions, octreotide has been used to treat the symptoms associated with metastatic carcinoid tumors (flushing and diarrhea), and VIP secreting adenomas (watery diarrhea).

12.2 Pharmacodynamics

Octreotide substantially reduces GH and/or IGF-1 (somatomedin C) levels in patients with acromegaly.

Single doses of octreotide have been shown to inhibit gallbladder contractility and to decrease bile secretion in normal volunteers. In controlled clinical trials, the incidence of gallstone or biliary sludge formation was markedly increased [see Warnings and Precautions (5.2)].

Octreotide suppresses secretion of TSH.

12.3 Pharmacokinetics

Absorption

After subcutaneous injection, octreotide is absorbed rapidly and completely from the injection site. Peak concentrations of 5.2 ng/mL (100-mcg dose) were reached 0.4 hours after dosing. Using a specific radioimmunoassay, IV and subcutaneous doses were found to be bioequivalent. Peak concentrations and area under the curve (AUC) values were dose proportional after IV single doses up to 200 mcg and subcutaneous single doses up to 500 mcg and after subcutaneous multiple doses up to 500 mcg 3 times a day (1,500 mcg/day). In patients with acromegaly, a mean peak concentration of 2.8 ng/mL (100-mcg dose) was reached in 0.7 hours after subcutaneous dosing.

Distribution

In healthy volunteers, the distribution of octreotide from plasma was rapid (tα½ = 0.2 h), the volume of distribution (Vdss) was estimated to be 13.6 L, and the total body clearance ranged from 7 L/hr to 10 L/hr. In blood, the distribution into the erythrocytes was found to be negligible and about 65% was bound in the plasma in a concentration-independent manner. Binding was mainly to lipoprotein and, to a lesser extent, to albumin. In patients with acromegaly, the volume of distribution (Vdss) was estimated to be 21.6 ± 8.5 L, and the total body clearance was increased to 18 L/h. The mean percent of the drug bound was 41.2%.

Elimination

The elimination of octreotide from plasma had an apparent half-life of 1.7 to 1.9 hours compared with 1 to 3 minutes with the natural hormone. The duration of action of Sandostatin Injection is variable but extends up to 12 hours depending upon the type of tumor. About 32% of the dose is excreted unchanged into the urine. In an elderly population, dose adjustments may be necessary due to a significant increase in the half-life (46%) and a significant decrease in the clearance (26%) of the drug.

In patients with acromegaly, the disposition and elimination half-lives were similar to normal subjects.

Specific Populations

Renal Impairment

In patients with mild renal impairment (CLCR 40 to 60 mL/min), octreotide t1/2 was 2.4 hours and total body clearance was 8.8 L/hr, in moderate impairment (CLCR 10 to 39 mL/min) t1/2 was 3.0 hours and total body clearance 7.3 L/hr. In patients with severe renal impairment not requiring dialysis (CLCR < 10 mL/min), octreotide t1/2 was 3.1 hours and total body clearance was 7.6 L/hr. In patients with severe renal failure requiring dialysis, total body clearance was reduced to about half that found in healthy subjects (from approximately 10 L/hr to 4.5 L/hr).

Hepatic Impairment

Patients with liver cirrhosis showed prolonged elimination of drug, with octreotide t1/2 increasing to 3.7 hr and total body clearance decreasing to 5.9 L/hr, whereas patients with fatty liver disease showed t1/2 increased to 3.4 hr and total body clearance of 8.2 L/hr.

12.6 Immunogenicity

Evaluation of 20 patients treated for at least 6 months has failed to demonstrate titers of antibodies exceeding background levels. However, antibody titers to Sandostatin Injection were subsequently reported in 3 patients and resulted in prolonged duration of drug action in 2 patients.

13 NONCLINICAL TOXICOLOGY

13.1 Carcinogenesis, Mutagenesis, Impairment of Fertility

Studies in laboratory animals have demonstrated no mutagenic potential of Sandostatin Injection.

No carcinogenic potential was demonstrated in mice treated subcutaneously for 85 to 99 weeks at doses up to 2,000 mcg/kg/day (8 x the human exposure based on BSA). In a 116-week subcutaneous study in rats, a 27% and 12% incidence of injection-site sarcomas or squamous cell carcinomas was observed in males and females, respectively, at the highest dose level of 1,250 mcg/kg/day (10 x the human exposure based on BSA) compared to an incidence of 8% to 10% in the vehicle-control groups. The increased incidence of injection-site tumors was most probably caused by irritation and the high sensitivity of the rat to repeated subcutaneous injections at the same site. Rotating injection sites would prevent chronic irritation in humans. There have been no reports of injection-site tumors in patients treated with Sandostatin for up to 5 years. There was also a 15% incidence of uterine adenocarcinomas in the 1,250 mcg/kg/day females compared to 7% in the saline-control females and 0% in the vehicle-control females. The presence of endometritis coupled with the absence of corpora lutea, the reduction in mammary fibroadenomas, and the presence of uterine dilatation suggest that the uterine tumors were associated with estrogen dominance in the aged female rats which does not occur in humans.

Octreotide did not impair fertility in rats at doses up to 1,000 mcg/kg/day, which represents 7-times the human exposure based on BSA.

16 HOW SUPPLIED/STORAGE AND HANDLING

How Supplied

Sandostatin (octreotide acetate) Injection is available in 1 mL ampuls as follows:

Ampuls

50 mcg/mL octreotide (as acetate)

Package of 10 ampuls ...........................................................................................................................................NDC 0078-0180-01

100 mcg/mL octreotide (as acetate)

Package of 10 ampuls ...........................................................................................................................................NDC 0078-0181-01

500 mcg/mL octreotide (as acetate)

Package of 10 ampuls ...........................................................................................................................................NDC 0078-0182-01

Storage and Handling

For prolonged storage, Sandostatin ampuls should be stored at refrigerated temperatures 2°C to 8°C (36°F to 46°F) and store in outer carton in order to protect from light. At room temperature (20°C to 30°C or 70°F to 86°F), Sandostatin is stable for 14 days if protected from light. The solution can be allowed to come to room temperature prior to administration. Do not warm artificially. Ampuls should be opened just prior to administration and the unused portion discarded. Dispose unused product or waste properly. Sandostatin Injection is stable in sterile isotonic saline solutions or sterile solutions of dextrose 5% in water for 24 hours.

17 PATIENT COUNSELING INFORMATION

Sterile Subcutaneous Injection Technique

Careful instruction in sterile subcutaneous injection technique should be given to the patients and to other persons who may administer Sandostatin Injection.

Cholelithiasis and Complications of Cholelithiasis

Advise patients to contact their healthcare provider if they experience signs or symptoms of gallstones (cholelithiasis) or complications of cholelithiasis (e.g., cholecystitis, cholangitis, and pancreatitis) [see Warnings and Precautions (5.2)].

Steatorrhea and Malabsorption of Dietary Fats

Advise patients to contact their healthcare provider if they experience new or worsening of steatorrhea, stool discoloration, loose stools, abdominal bloating, and weight loss [see Warnings and Precautions (5.5)].

Pregnancy

Inform female patients that treatment with Sandostatin Injection may result in unintended pregnancy [see Use in Specific Populations (8.3)].

Distributed by:
Novartis Pharmaceuticals Corporation
East Hanover, New Jersey 07936

© Novartis

T2024-50

PRINCIPAL DISPLAY PANEL

NDC 0078-0180-01
Unit Dose Package

Sandostatin®

octreotide acetate

INJECTION

Rx only

50 mcg/mL

For Subcutaneous or Intravenous Use

10 Ampuls/1 mL size

NOVARTIS

PRINCIPAL DISPLAY PANEL

NDC 0078-0181-01
Unit Dose Package

Sandostatin®

octreotide acetate

INJECTION

Rx only

100 mcg/mL

For Subcutaneous or Intravenous Use

10 Ampuls/1 mL size

NOVARTIS

PRINCIPAL DISPLAY PANEL

NDC 0078-0182-01
Unit Dose Package

Sandostatin®

octreotide acetate

INJECTION

Rx only

500 mcg/mL

For Subcutaneous or Intravenous Use

10 Ampuls/1 mL size

NOVARTIS